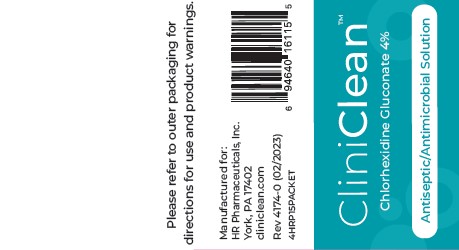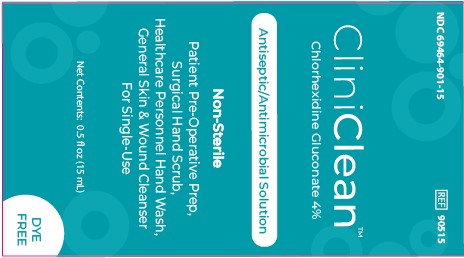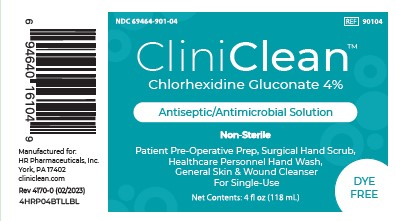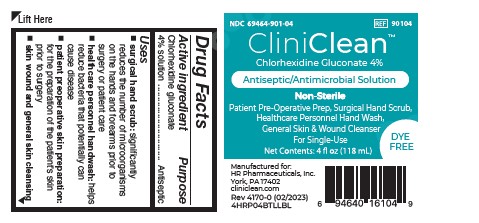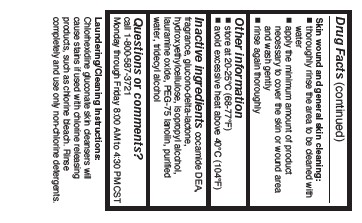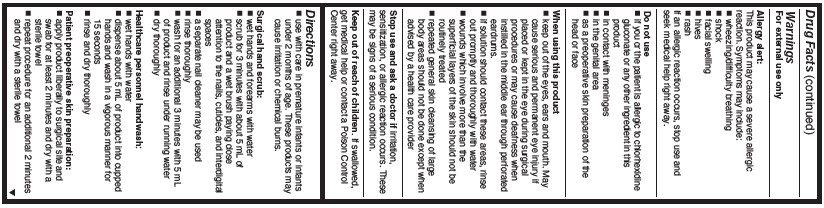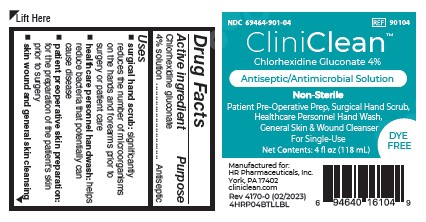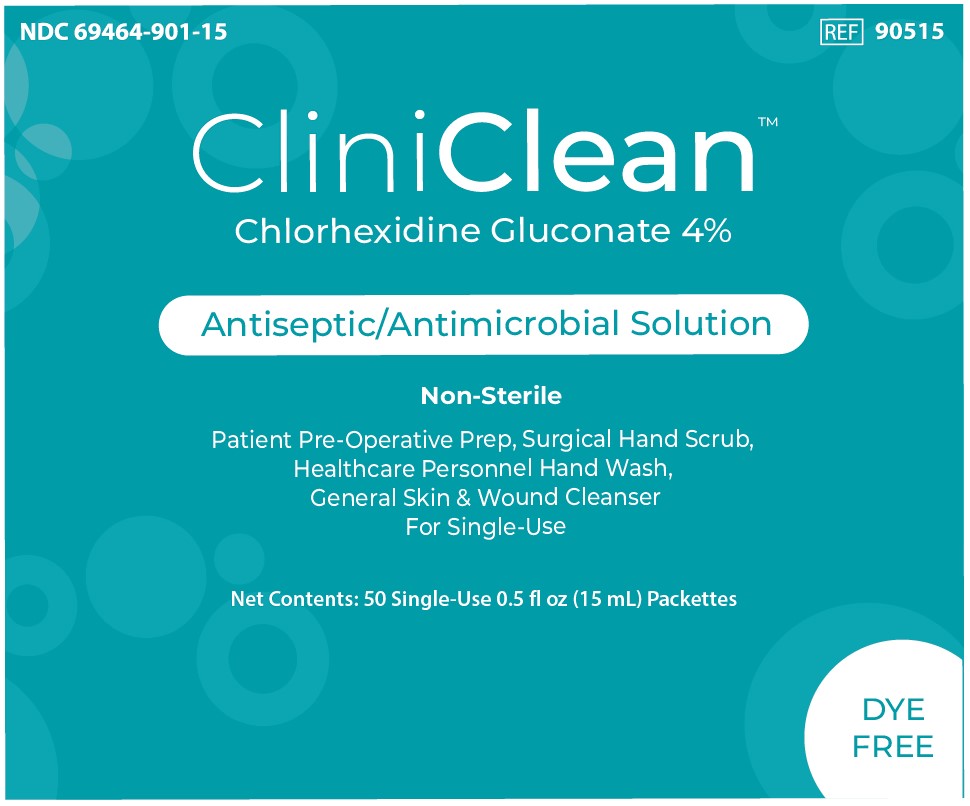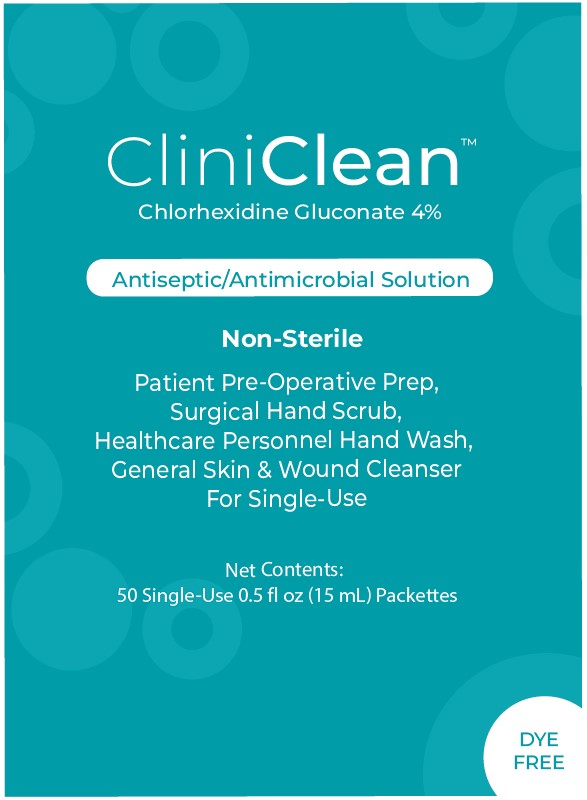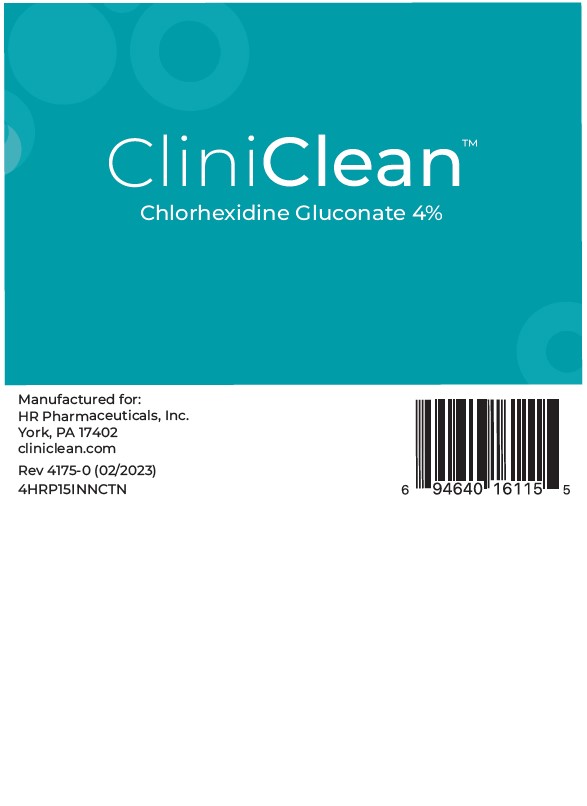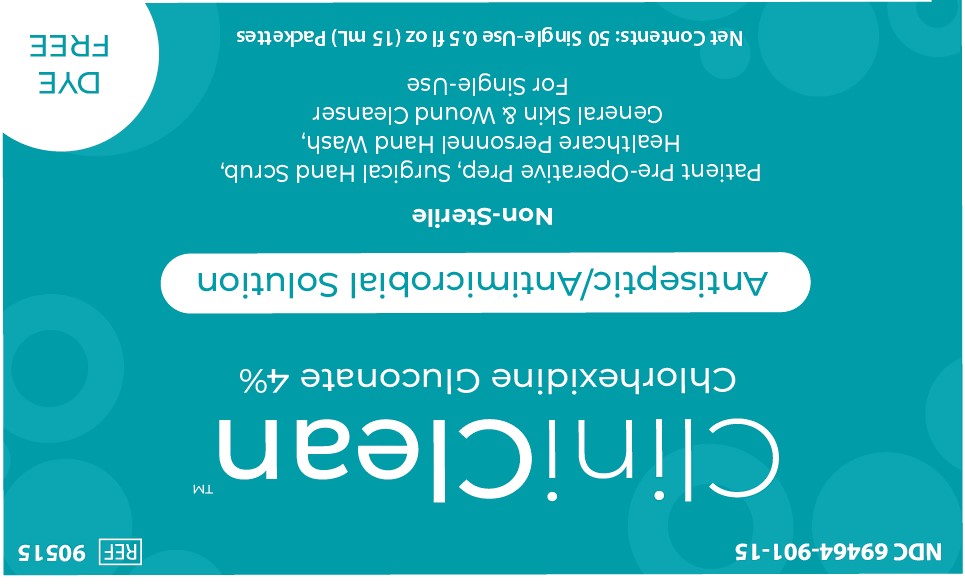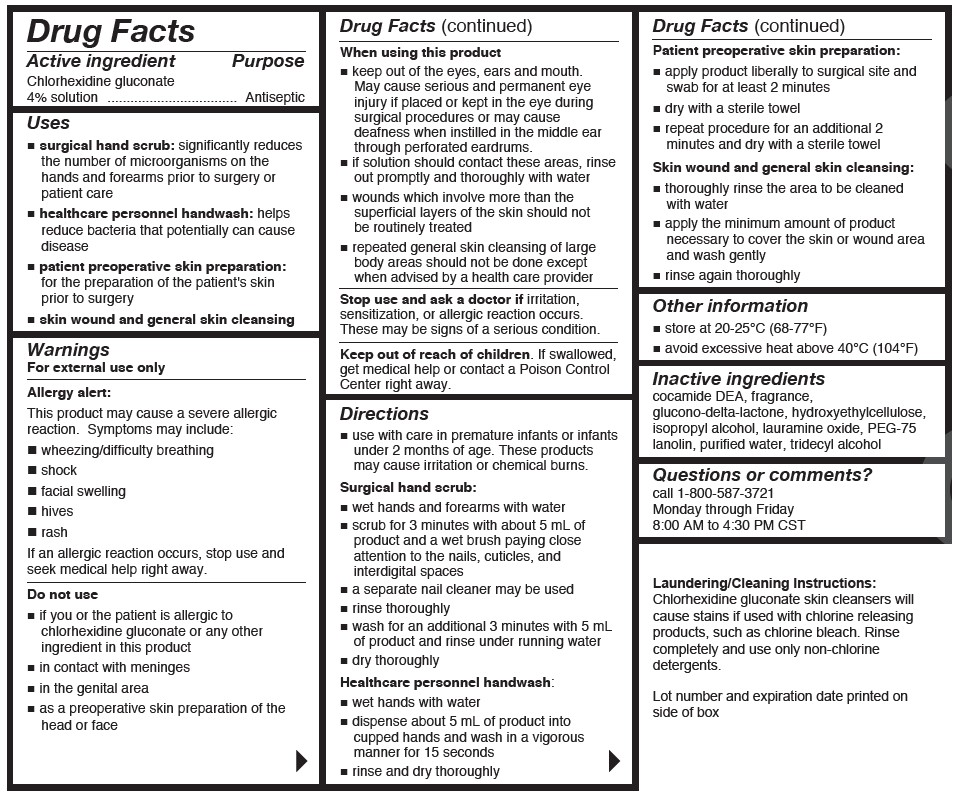 DRUG LABEL: CliniClean
NDC: 69464-901 | Form: SOLUTION
Manufacturer: HR Pharmaceuticals, Inc.
Category: otc | Type: HUMAN OTC DRUG LABEL
Date: 20251216

ACTIVE INGREDIENTS: CHLORHEXIDINE GLUCONATE 4 g/100 mL
INACTIVE INGREDIENTS: PEG-75 LANOLIN; HYDROXYETHYL CELLULOSE (2000 CPS AT 1%); WATER; TRIDECYL ALCOHOL; GLUCONOLACTONE; ISOPROPYL ALCOHOL; COCO DIETHANOLAMIDE; LAURAMINE OXIDE

4% HR Pharma 15 mL Packets, 15mL Carton,
COMP 4oz

Active ingredient

Chlorhexidine gluconate 4% solution

Purpose

Antiseptic

Uses

- surgical hand scrub: significantly reduces the number of microorganisms on the hands and forearms prior to surgery or patient care
- healthcare personnel handwash: helps reduce bacteria that potentially can cause disease
- patient preoperative skin preparation: for the preparation of the patient's skin prior to surgery
- skin wound and general skin cleansing

Warnings

For external use only

Allergy alert:

This product may cause a severe allergic reaction.Symptoms may include:

- wheezing/difficulty breathing
- shock
- facial swelling
- hives
- rash

If an allergic reaction occurs, stop use and seek medical help right away.

Do not use

- if you or the patient is allergic to chlorhexidine gluconate or any other ingredient in this product
- in contact with the meninges
- in the genital area

When using this product

- keep out of eyes, ears and mouth. May cause serious and permanent eye injury if placed or kept in the eye during surgical procedures or may cause deafness when instilled in the middle ear through perforated eardurms.
- if solution should contact these areas, rinse out promptly and thoroughly with water
- wounds which involve more than the superficial layers of the skin should not be routinely treated
- repeated general skin cleansing of large body areas should not be done except when advised by a healthcare provider

Stop use and ask a doctor if

irritation, sensitization, or allergic reaction occurs. These may be signs of a serious condition.

Keep out of reach of children

If swallowed, get medical help or contact a Poison Control Center right away.

Directions

- use with care in premature infants or infants under 2 months of age. These products may cause irritation or chemical burns.

Surgical hand scrub:

- wet hands and forearms with water
- scrub for 3 minutes with about 5mL of product and a wet brush paying close attention to the nails, cuticles, and interdigital spaces
- a seperate nail cleaner may be used
- rinse thoroughly
- wash for an additional 3 minutes with 5mL of product and rinse under running water
- dry thoroughly

Healthcare personnel handwash:

- wet hands with water
- dispense about 5mL of product into cupped hands and wash in a vigrous manner for 15 seconds
- rinse and dry thoroughly

Patient preoperative skin preparation:

- apply product liberally to surgical site and swab for at least 2 minutes
- dry with a sterile towel
- repeat procedure for an additional 2 minutes and dry with a sterile towel

Skin wound and general skin cleansing:

- thoroughly rinse the area to be cleaned with water
- apply the minimum amount of product necessary to cover the skin or wound area and wash gently
- rinse again thoroughly

Other information

- store at 20-25°C (68-77°F)
- avoid excessive heat above 40°C (104°F)

Inactive ingredients

cocamide DEA, fragrance, glucono-delta-lactone, hydroxyethylcellulose, isopropyl alcohol, lauramine oxide, PEG-75 lanolin, purified water, tridecyl alcohol

Questions or comments?

call 1-800-587-3721 Monday through Friday 8:00 AM to 4:30 PM CST

Laudering/Cleaning Instructions

Chlorhexidine gluconate skin cleansers will cause stains if used with chlorine releasing products, such as chlorine bleach. Rinse completely and use only non-chlorine detergents.

Display Panels

NDC 69494-901-04

REF 90104

CliniClean

Chlorhexidine Gluconate 4%

Antispetic/Antimicrobial Solution

Non-Sterile

Patient Pre-Operative Prep, Surgical Hand Scrub, Healthcare Personnel Hand Wash. General Skin & Wound Cleanser

For Single-Use

Net Content: 4 fl oz (118mL)

DYE FREE

Manufactured for:

HR Pharmaceuticals, Inc.

York, PA 17402

cliniclean.com

Rev 4170-0 (02/2023)

4HRP04BTLLBL

NDC 69494-901-15

REF 901515

CliniClean

Chlorhexidine Gluconate 4%

Antispetic/Antimicrobial Solution

Non-Sterile

Patient Pre-Operative Prep, Surgical Hand Scrub, Healthcare Personnel Hand Wash. General Skin & Wound Cleanser

For Single-Use

Net Contents: 50 Single-Use 0.5 fl oz (15 mL) Packettes

DYE FREE

Manufactured for:

HR Pharmaceuticals, Inc.

York, PA 17402

cliniclean.com

Rev 4175-0 (02/2023)

4HRP15INNCTN

4HRP15PACKET